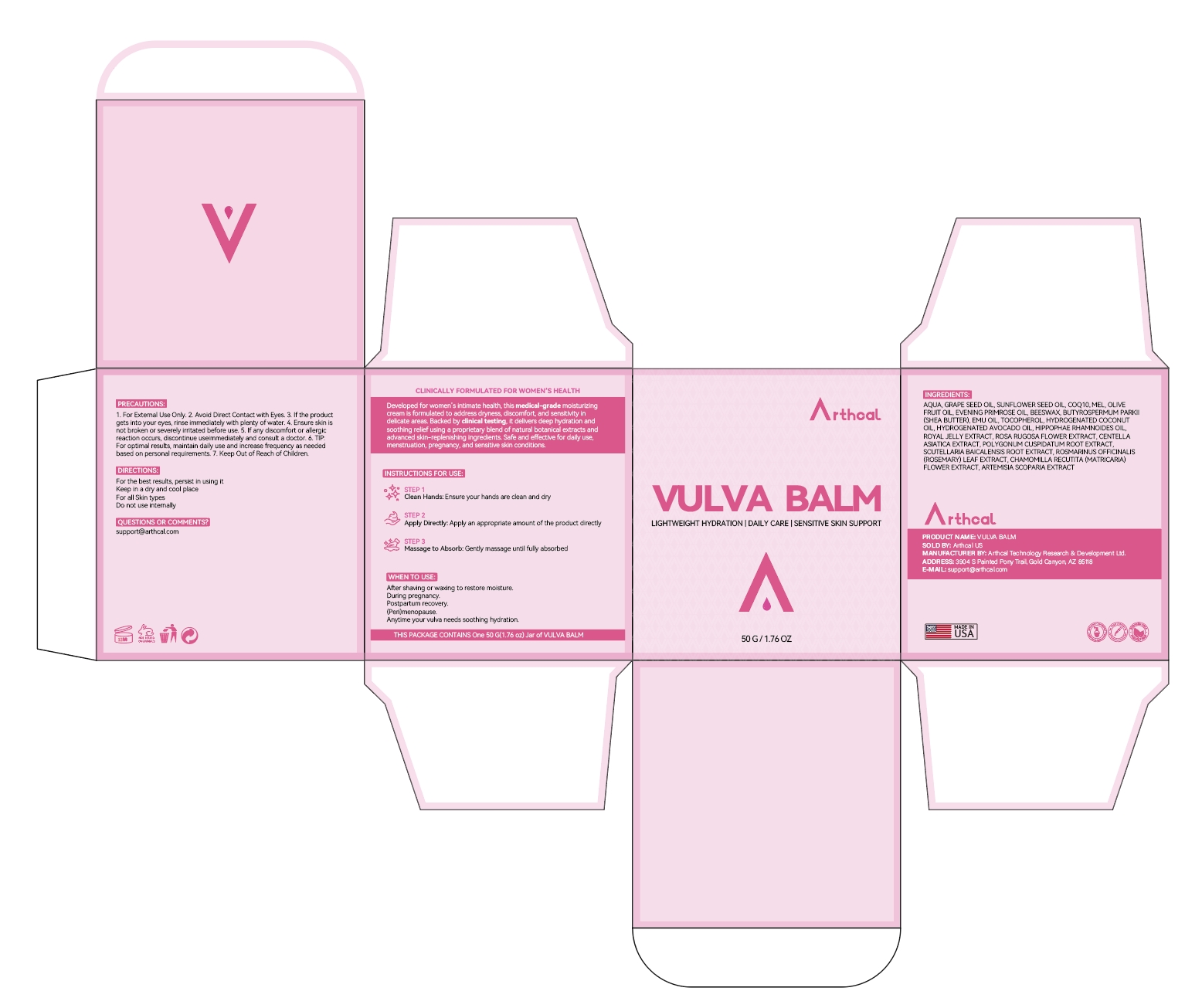 DRUG LABEL: Arthcal VULVA BALM
NDC: 85212-0024 | Form: CREAM
Manufacturer: Beijing JUNGE Technology Co., Ltd.
Category: otc | Type: HUMAN OTC DRUG LABEL
Date: 20250311

ACTIVE INGREDIENTS: BEESWAX 5 g/100 g; GRAPE SEED OIL 5 g/100 g; SHEA BUTTER 5 g/100 g
INACTIVE INGREDIENTS: MATRICARIA CHAMOMILLA FLOWERING TOP OIL 0.2 g/100 g; SUNFLOWER SEED 5 g/100 g; HONEY 5 g/100 g; EVENING PRIMROSE OIL 2 g/100 g; EMU OIL 1.5 g/100 g; TOCOPHEROL 0.5 g/100 g; HYDROGENATED COCONUT OIL 0.5 g/100 g; HYDROGENATED AVOCADO OIL 0.5 g/100 g; AQUA 63 g/100 g; ROYAL JELLY 0.5 g/100 g; ROSA RUGOSA FLOWER 0.5 g/100 g; CENTELLA ASIATICA 0.5 g/100 g; POLYGONUM CUSPIDATUM ROOT 0.5 g/100 g; SCUTELLARIA BAICALENSIS ROOT 0.5 g/100 g; ROSEMARY 0.2 g/100 g; ARTEMISIA SCOPARIA WHOLE 0.2 g/100 g; OLIVE OIL 3.4 g/100 g; LAMINARIA DIGITATA 0.5 g/100 g

DOSAGE AND ADMINISTRATION

50g(1.76oz)

INDICATIONS AND USAGE

Clean Hands: Ensure your hands are clean and dry.

Apply Directly: Apply an appropriate amount of the productectly.

Massage to Absorb:Gently massage until fully absorbed.

INACTIVE INGREDIENT

AQUA
SUNFLOWER SEED OIL
MEL
OLIVE FRUIT OIL
EVENING PRIMROSE OIL
EMU OIL
TOCOPHEROL
HYDROGENATED COCONUT OIL
HYDROGENATED AVOCADO OIL
HIPPOPHAE RHAMNOIDES OIL
ROYAL JELLY EXTRACT
ROSA RUGOSA FLOWER EXTRACT
CENTELLA ASIATICA EXTRACT
POLYGONUM CUSPIDATUM ROOT EXTRACT
SCUTELLARIA BAICALENSIS ROOT EXTRACT
ROSMARINUS OFFICINALIS (ROSEMARY) LEAF EXTRACT
CHAMOMILLA RECUTITA (MATRICARIA) FLOWER EXTRACT
ARTEMISIA SCOPARIA EXTRACT

PURPOSE

Address dryness, discomfort, and sensitivity in delicate areas.

Keep Out of Reach of Children.

WARNINGS

1. For Extemal Use Only. 2. Avoid Direct Contact with Eyes. 3. If the product
gets into your eyes, rinse immediately with plenty of water. 4. Ensure skin is
not broken or severely irritated before use. 5. If any discomfort or allergic
reaction occurs, discontinue use immediately and consult a doctor.6. TIP
For optimal results, maintain daily use and increase frequency as needed
based on personal requirements. 7. Keep Out of Reach of Children.